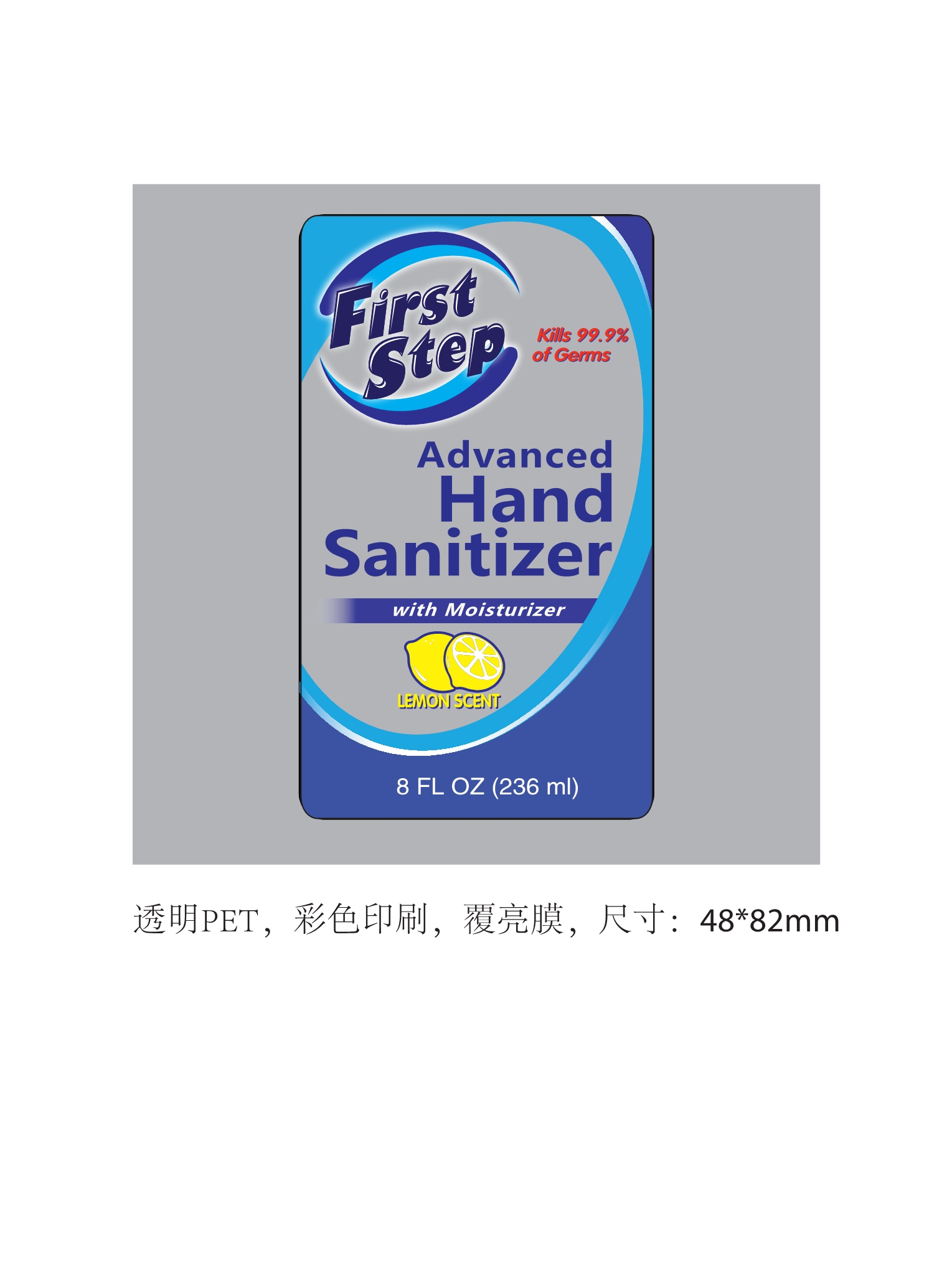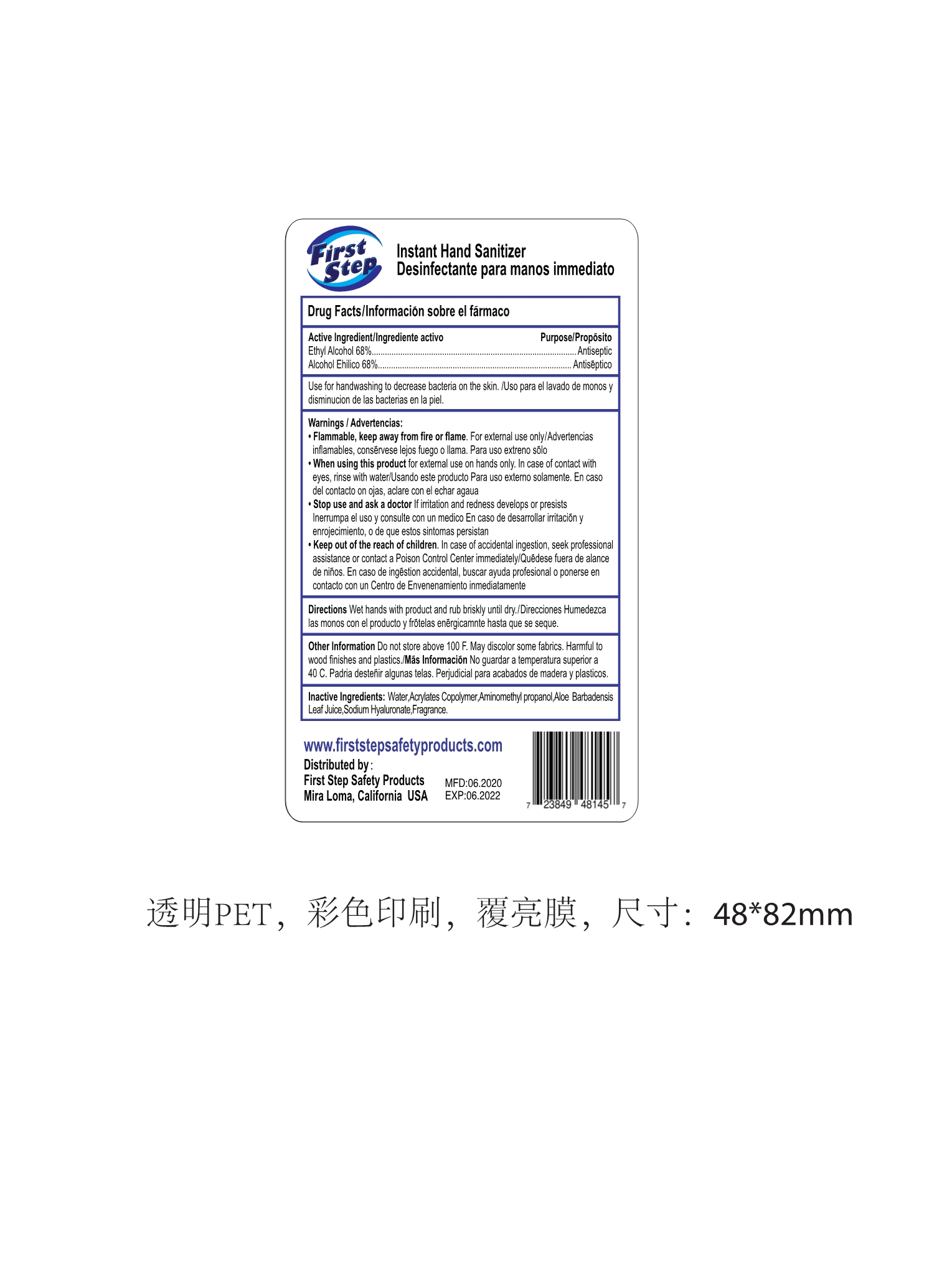 DRUG LABEL: Hand Sanitizer
NDC: 79195-001 | Form: GEL
Manufacturer: First Step Safety Products Corporation
Category: otc | Type: HUMAN OTC DRUG LABEL
Date: 20200704

ACTIVE INGREDIENTS: ALCOHOL 68 mL/100 mL
INACTIVE INGREDIENTS: HYALURONATE SODIUM; BUTYL ACRYLATE/METHYL METHACRYLATE/METHACRYLIC ACID COPOLYMER (18000 MW); AMINOMETHYLPROPANOL; WATER; ALOE VERA LEAF; LEMON

First Step Safety Products Corporation
236mL Hand Sanitizer
79195-001-01

Active Ingredient(s)

Alcohol 68% v/v.

Purpose

Antiseptic, Hand Sanitizer

Use

Use for handwashing to decrease bacteria on the skin.

Warnings

Flammable, keep away from fire or flame. For external use only.

Do not use

- in children less than 2 months of age
- on open skin wounds

When using this product for external use on hands only. In case of contact with eyes, rinse with water.

Stop use and ask a doctor If irritation and redness develops or presists.

KEEP OUT OF REACH OF CHILDREN

Keep out of the reach of children. In case of accidental ingestion, seek professional assistance or contact a Poison Control Center immediately.

Directions

Wet hands with product and rub briskly until dry.

OTHER SAFETY INFORMATION

Do not store above 100F.
May discolor some fabrics.
Harmful to wood finishes and plastics.

Inactive ingredients

Water, Acrylates Copolymer, Aminomethyl propanol, Aloe Barbadensis Leaf Juice, Sodium Hyaluronate, Fragrance

Package Label - Principal Display Panel

236 mL in 1 BOTTLE NDC: 79195-001-01